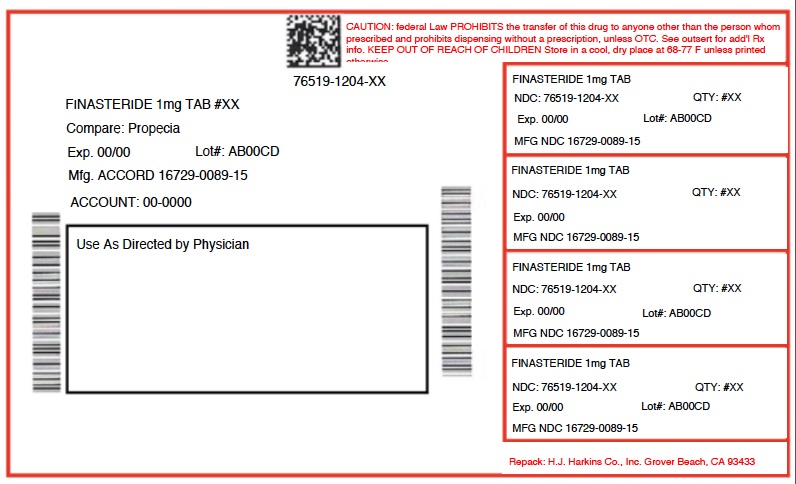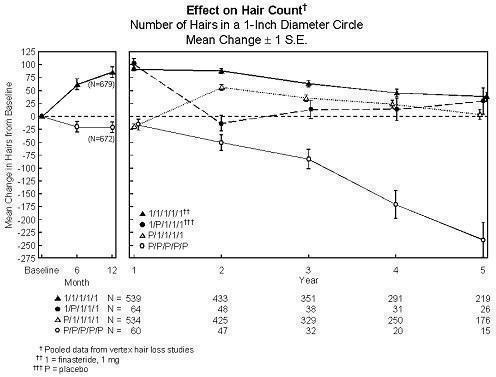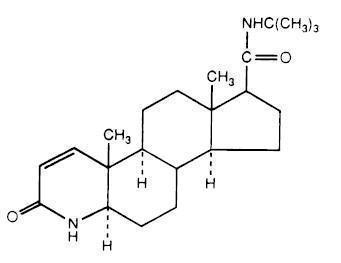 DRUG LABEL: FINASTERIDE
NDC: 76519-1204 | Form: TABLET, FILM COATED
Manufacturer: H.J. Harkins Company, Inc.
Category: prescription | Type: HUMAN PRESCRIPTION DRUG LABEL
Date: 20180824

ACTIVE INGREDIENTS: FINASTERIDE 1 mg/1 1

1204

INDICATIONS AND USAGE

- Finasteride tablets are indicated for the treatment of male pattern hair loss (androgenetic alopecia) inMEN ONLY.
- Efficacy in bitemporal recession has not been established.
- Finasteride tablets are not indicated for use in women.

DOSAGE AND ADMINISTRATION

- Finasteride tablets may be administered with or without meals.
- The recommended dose of finasteride tablets is one tablet (1 mg) taken once daily.
- In general, daily use for three months or more is necessary before benefit is observed. Continued use is recommended to sustain benefit, which should be re-evaluated periodically. Withdrawal of treatment leads to reversal of effect within 12 months.

DOSAGE FORMS AND STRENGTHS

- Finasteride tablets, USP 1 mg are reddish brown, 7 mm, round, biconvex, film coated tablets, marked ‘F1’ on one side and plain on other side.

CONTRAINDICATIONS

Finasteride is contraindicated in the following:

- Pregnancy. Finasteride use is contraindicated in women when they are or may potentially be pregnant. Because of the ability of Type II 5α-reductase inhibitors to inhibit the conversion of testosterone to 5α-dihydrotestosterone (DHT), finasteride may cause abnormalities of the external genitalia of a male fetus of a pregnant woman who receives finasteride. If this drug is used during pregnancy, or if pregnancy occurs while taking this drug, the pregnant woman should be apprised of the potential hazard to the male fetus. [See WARNINGS AND PRECAUTIONS (5.1), USE IN SPECIFIC POPULATIONS (8.1), HOW SUPPLIED/STORAGE AND HANDLING (16) and PATIENT COUNSELING INFORMATION (17.1).] In female rats, low doses of finasteride administered during pregnancy have produced abnormalities of the external genitalia in male offspring.

- Hypersensitivity to any component of this medication.

WARNINGS AND PRECAUTIONS

5.1 Exposure of Women — Risk to Male Fetus

Finasteride is not indicated for use in women. Women should not handle crushed or broken finasteride tablets when they are pregnant or may potentially be pregnant because of the possibility of absorption of finasteride and the subsequent potential risk to a male fetus. Finasteride tablets are coated and will prevent contact with the active ingredient during normal handling, provided that the tablets have not been broken or crushed. [See INDICATIONS AND USAGE (1), CONTRAINDICATIONS (4), USE IN SPECIFIC POPULATIONS (8.1), HOW SUPPLIED/STORAGE AND HANDLING (16) and PATIENT COUNSELING INFORMATION (17.1).]

5.2 Effects on Prostate Specific Antigen (PSA)

In clinical studies with finasteride, 1 mg in men 18 to 41 years of age, the mean value of serum prostate specific antigen (PSA) decreased from 0.7 ng/mL at baseline to 0.5 ng/mL at Month 12. Further, in clinical studies with finasteride, 5 mg when used in older men who have benign prostatic hyperplasia (BPH), PSA levels are decreased by approximately 50%. Other studies with finasteride, 5 mg showed it may also cause decreases in serum PSA in the presence of prostate cancer. These findings should be taken into account for proper interpretation of serum PSA when evaluating men treated with finasteride. Any confirmed increase from the lowest PSA value while on finasteride 1 mg may signal the presence of prostate cancer and should be evaluated, even if PSA levels are still within the normal range for men not taking a 5α-reductase inhibitor. Non-compliance to therapy with finasteride 1 mg may also affect PSA test results.

5.3 Increased Risk of High-Grade Prostate Cancer with 5α-Reductase Inhibitors

Men aged 55 and over with a normal digital rectal examination and PSA ≤3.0 ng/mL at baseline taking finasteride 5 mg/day (5 times the dose of finasteride 1 mg) in the 7-year Prostate Cancer Prevention Trial (PCPT) had an increased risk of Gleason score 8 to 10 prostate cancer (finasteride 1.8% vs placebo 1.1%). [See ADVERSE REACTIONS (6.1). ] Similar results were observed in a 4-year placebo-controlled clinical trial with another 5α-reductase inhibitor (dutasteride, AVODART) (1% dutasteride vs 0.5% placebo). 5α-reductase inhibitors may increase the risk of development of high-grade prostate cancer. Whether the effect of 5α-reductase inhibitors to reduce prostate volume, or study-related factors, impacted the results of these studies has not been established.

5.4 Pediatric Patients

Finasteride is not indicated for use in pediatric patients [see USE IN SPECIFIC POPULATIONS (8.4)] .

DRUG INTERACTIONS

7.1 Cytochrome P450-Linked Drug Metabolizing Enzyme System

No drug interactions of clinical importance have been identified. Finasteride does not appear to affect the cytochrome P450-linked drug-metabolizing enzyme system. Compounds that have been tested in man include antipyrine, digoxin, propranolol, theophylline, and warfarin and no clinically meaningful interactions were found.

7.2 Other Concomitant Therapy

Although specific interaction studies were not performed, finasteride doses of 1 mg or more were concomitantly used in clinical studies with acetaminophen, acetylsalicylic acid, α-blockers, analgesics, angiotensin-converting enzyme (ACE) inhibitors, anticonvulsants, benzodiazepines, beta blockers, calcium-channel blockers, cardiac nitrates, diuretics, H 2 antagonists, HMG-CoA reductase inhibitors, prostaglandin synthetase inhibitors (also referred to as NSAIDs), and quinolone anti-infectives without evidence of clinically significant adverse interactions.

USE IN SPECIFIC POPULATIONS

8.1 Pregnancy

Pregnancy Category X [see CONTRAINDICATIONS (4)].

Finasteride is contraindicated for use in women who are or may become pregnant. Finasteride is a Type II 5α-reductase inhibitor that prevents conversion of testosterone to 5α-dihydrotestosterone (DHT), a hormone necessary for normal development of male genitalia. In animal studies, finasteride caused abnormal development of external genitalia in male fetuses. If this drug is used during pregnancy, or if the patient becomes pregnant while taking this drug, the patient should be apprised of the potential hazard to the male fetus.

Abnormal male genital development is an expected consequence when conversion of testosterone to 5α-dihydrotestosterone (DHT) is inhibited by 5α-reductase inhibitors. These outcomes are similar to those reported in male infants with genetic 5α-reductase deficiency. Women could be exposed to finasteride through contact with crushed or broken finasteride tablets or semen from a male partner taking finasteride. With regard to finasteride exposure through the skin, finasteride tablets are coated and will prevent skin contact with finasteride during normal handling if the tablets have not been crushed or broken. Women who are pregnant or may become pregnant should not handle crushed or broken finasteride tablets because of possible exposure of a male fetus. If a pregnant woman comes in contact with crushed or broken finasteride tablets, the contact area should be washed immediately with soap and water. With regard to potential finasteride exposure through semen, a study has been conducted in men receiving finasteride 1 mg/day that measured finasteride concentrations in semen[see CLINICAL PHARMACOLOGY (12.3)].

In an embryo-fetal development study, pregnant rats received finasteride during the period of major organogenesis (gestation days 6 to 17). At maternal doses of oral finasteride approximately 1 to 684 times the recommended human dose (RHD) of 1 mg/day (based on AUC at animal doses of 0.1 to 100 mg/kg/day) there was a dose-dependent increase in hypospadias that occurred in 3.6 to 100% of male offspring. Exposure multiples were estimated using data from nonpregnant rats. Days 16 to 17 of gestation is a critical period in male fetal rats for differentiation of the external genitalia. At oral maternal doses approximately 0.2 times the RHD (based on AUC at animal dose of 0.03 mg/kg/day), male offspring had decreased prostatic and seminal vesicular weights, delayed preputial separation and transient nipple development. Decreased anogenital distance occurred in male offspring of pregnant rats that received approximately 0.02 times the RHD (based on AUC at animal dose of 0.003 mg/kg/day). No abnormalities were observed in female offspring exposed to any dose of finasteride in utero.

No developmental abnormalities were observed in the offspring of untreated females mated with finasteride-treated male rats that received approximately 488 times the RHD (based on AUC at animal dose of 80 mg/kg/day). Slightly decreased fertility was observed in male offspring after administration of about 20 times the RHD (based on AUC at animal dose of 3 mg/kg/day) to female rats during late gestation and lactation. No effects on fertility were seen in female offspring under these conditions.

No evidence of male external genital malformations or other abnormalities were observed in rabbit fetuses exposed to finasteride during the period of major organogenesis (gestation days 6 to 18) at maternal doses up to 100 mg/kg/day (finasteride exposure levels were not measured in rabbits). However, this study may not have included the critical period for finasteride effects on development of male external genitalia in the rabbit.

The fetal effects of maternal finasteride exposure during the period of embryonic and fetal development were evaluated in the rhesus monkey (gestation days 20 to 100), in a species and development period more predictive of specific effects in humans than the studies in rats and rabbits. Intravenous administration of finasteride to pregnant monkeys at doses as high as 800 ng/day (estimated maximal blood concentration of 1.86 ng/mL or about 930 times the highest estimated exposure of pregnant women to finasteride from semen of men taking 1 mg/day) resulted in no abnormalities in male fetuses. In confirmation of the relevance of the rhesus model for human fetal development, oral administration of a dose of finasteride (2 mg/kg/day or approximately 120,000 times the highest estimated blood levels of finasteride from semen of men taking 1 mg/day) to pregnant monkeys resulted in external genital abnormalities in male fetuses. No other abnormalities were observed in male fetuses and no finasteride-related abnormalities were observed in female fetuses at any dose.

8.3 Nursing Mothers

Finasteride is not indicated for use in women.

It is not known whether finasteride is excreted in human milk.

8.4 Pediatric Use

Finasteride is not indicated for use in pediatric patients.

Safety and effectiveness in pediatric patients have not been established.

8.5 Geriatric Use

Clinical efficacy studies with finasteride did not include subjects aged 65 and over. Based on the pharmacokinetics of finasteride 5 mg, no dosage adjustment is necessary in the elderly for finasteride[see CLINICAL PHARMACOLOGY (12.3)] . However the efficacy of finasteride in the elderly has not been established.

8.6 Hepatic Impairment

Caution should be exercised in the administration of finasteride in those patients with liver function abnormalities, as finasteride is metabolized extensively in the liver [see CLINICAL PHARMACOLOGY (12.3)].

8.7 Renal Impairment

No dosage adjustment is necessary in patients with renal impairment [see CLINICAL PHARMACOLOGY (12.3)] .

OVERDOSAGE

In clinical studies, single doses of finasteride up to 400 mg and multiple doses of finasteride up to 80 mg/day for three months did not result in adverse reactions. Until further experience is obtained, no specific treatment for an overdose with finasteride can be recommended.

Significant lethality was observed in male and female mice at single oral doses of 1500 mg/m 2 (500 mg/kg) and in female and male rats at single oral doses of 2360 mg/m 2 (400 mg/kg) and 5900 mg/m 2(1000 mg/kg), respectively.

DESCRIPTION

Finasteride tablets, USP contain finasteride as the active ingredient. Finasteride, a synthetic 4-azasteroid compound, is a specific inhibitor of steroid Type II 5α-reductase, an intracellular enzyme that converts the androgen testosterone into 5α-dihydrotestosterone (DHT).

The chemical name of finasteride is N-tert-Butyl-3-oxo-4-aza-5α-androst-1-ene-17β-carboxamide. The empirical formula of finasteride is C 23H 36N 2O 2 and its molecular weight is 372.55. Its structural formula is:

Finasteride is a white crystalline powder with a melting point near 250°C. It is freely soluble in chloroform and in lower alcohol solvents but is practically insoluble in water.

Finasteride tablets, USP are film-coated tablets for oral administration. Each tablet contains 1 mg of finasteride and the following inactive ingredients: lactose monohydrate, microcrystalline cellulose, pregelatinized starch (maize), sodium starch glycolate, lauroyl macrogolglycerides, magnesium stearate, hypromellose, titanium dioxide, polyethylene glycol, iron oxide red, and iron oxide yellow.

NONCLINICAL TOXICOLOGY

13.1 Carcinogenesis, Mutagenesis, Impairment of Fertility

No evidence of a tumorigenic effect was observed in a 24-month study in Sprague-Dawley rats receiving doses of finasteride up to 160 mg/kg/day in males and 320 mg/kg/day in females. These doses produced respective systemic exposure in rats of 888 and 2192 times those observed in man receiving the recommended human dose of 1 mg/day. All exposure calculations were based on calculated AUC (0-24 hr) for animals and mean AUC (0-24 hr) for man (0.05 µg∙hr/mL).

In a 19-month carcinogenicity study in CD-1 mice, a statistically significant (p≤0.05) increase in the incidence of testicular Leydig cell adenomas was observed at 1824 times the human exposure (250 mg/kg/day). In mice at 184 times the human exposure, estimated (25 mg/kg/day) and in rats at 312 times the human exposure (≥40 mg/kg/day) an increase in the incidence of Leydig cell hyperplasia was observed. A positive correlation between the proliferative changes in the Leydig cells and an increase in serum LH levels (2- to 3-fold above control) has been demonstrated in both rodent species treated with high doses of finasteride. No drug-related Leydig cell changes were seen in either rats or dogs treated with finasteride for 1 year at 240 and 2800 times (20 mg/kg/day and 45 mg/kg/day, respectively), or in mice treated for 19 months at 18.4 times the human exposure, estimated (2.5 mg/kg/day).

No evidence of mutagenicity was observed in an in vitro bacterial mutagenesis assay, a mammalian cell mutagenesis assay, or in an in vitro alkaline elution assay. In an in vitro chromosome aberration assay, using Chinese hamster ovary cells, there was a slight increase in chromosome aberrations. In an in vivochromosome aberration assay in mice, no treatment-related increase in chromosome aberration was observed with finasteride at the maximum tolerated dose of 250 mg/kg/day (1824 times the human exposure) as determined in the carcinogenicity studies.

In sexually mature male rabbits treated with finasteride at 4344 times the human exposure (80 mg/kg/day) for up to 12 weeks, no effect on fertility, sperm count, or ejaculate volume was seen. In sexually mature male rats treated with 488 times the human exposure (80 mg/kg/day), there were no significant effects on fertility after 6 or 12 weeks of treatment; however, when treatment was continued for up to 24 or 30 weeks, there was an apparent decrease in fertility, fecundity, and an associated significant decrease in the weights of the seminal vesicles and prostate. All these effects were reversible within 6 weeks of discontinuation of treatment. No drug-related effect on testes or on mating performance has been seen in rats or rabbits. This decrease in fertility in finasteride-treated rats is secondary to its effect on accessory sex organs (prostate and seminal vesicles) resulting in failure to form a seminal plug. The seminal plug is essential for normal fertility in rats but is not relevant in man.

14.1 Studies in Men

The efficacy of finasteride was demonstrated in men (88% Caucasian) with mild to moderate androgenetic alopecia (male pattern hair loss) between 18 and 41 years of age. In order to prevent seborrheic dermatitis which might confound the assessment of hair growth in these studies, all men, whether treated with finasteride or placebo, were instructed to use a specified, medicated, tar-based shampoo (Neutrogena T/Gel ® Shampoo) during the first 2 years of the studies.

There were three double-blind, randomized, placebo-controlled studies of 12-month duration. The two primary endpoints were hair count and patient self-assessment; the two secondary endpoints were investigator assessment and ratings of photographs. In addition, information was collected regarding sexual function (based on a self-administered questionnaire) and non-scalp body hair growth. The three studies were conducted in 1879 men with mild to moderate, but not complete, hair loss. Two of the studies enrolled men with predominantly mild to moderate vertex hair loss (n=1553). The third enrolled men having mild to moderate hair loss in the anterior mid-scalp area with or without vertex balding (n=326).

Studies in Men with Vertex Baldness

Of the men who completed the first 12 months of the two vertex baldness trials, 1215 elected to continue in double-blind, placebo-controlled, 12-month extension studies. There were 547 men receiving finasteride for both the initial study and first extension periods (up to 2 years of treatment) and 60 men receiving placebo for the same periods. The extension studies were continued for 3 additional years, with 323 men on finasteride and 23 on placebo entering the fifth year of the study.

In order to evaluate the effect of discontinuation of therapy, there were 65 men who received finasteride for the initial 12 months followed by placebo in the first 12-month extension period. Some of these men continued in additional extension studies and were switched back to treatment with finasteride, with 32 men entering the fifth year of the study. Lastly, there were 543 men who received placebo for the initial 12 months followed by finasteride in the first 12-month extension period. Some of these men continued in additional extension studies receiving finasteride, with 290 men entering the fifth year of the study (see FIGURE 1 below).

Hair counts were assessed by photographic enlargements of a representative area of active hair loss. In these two studies in men with vertex baldness, significant increases in hair count were demonstrated at 6 and 12 months in men treated with finasteride, while significant hair loss from baseline was demonstrated in those treated with placebo. At 12 months there was a 107-hair difference from placebo (p<0.001, finasteride [n=679] vs placebo [n=672]) within a 1-inch diameter circle (5.1 cm 2). Hair count was maintained in those men taking finasteride for up to 2 years, resulting in a 138-hair difference between treatment groups (p<0.001, finasteride [n=433] vs placebo [n=47]) within the same area. In men treated with finasteride, the maximum improvement in hair count compared to baseline was achieved during the first 2 years. Although the initial improvement was followed by a slow decline, hair count was maintained above baseline throughout the 5 years of the studies. Furthermore, because the decline in the placebo group was more rapid, the difference between treatment groups also continued to increase throughout the studies, resulting in a 277-hair difference (p<0.001, finasteride [n=219] vs placebo [n=15]) at 5 years (see FIGURE 1 below).

Patients who switched from placebo to finasteride (n=425) had a decrease in hair count at the end of the initial 12-month placebo period, followed by an increase in hair count after 1 year of treatment with finasteride. This increase in hair count was less (56 hairs above original baseline) than the increase (91 hairs above original baseline) observed after 1 year of treatment in men initially randomized to finasteride. Although the increase in hair count, relative to when therapy was initiated, was comparable between these two groups, a higher absolute hair count was achieved in patients who were started on treatment with finasteride in the initial study. This advantage was maintained through the remaining 3 years of the studies. A change of treatment from finasteride to placebo (n=48) at the end of the initial 12 months resulted in reversal of the increase in hair count 12 months later, at 24 months (see FIGURE 1 below).

At 12 months, 58% of men in the placebo group had further hair loss (defined as any decrease in hair count from baseline), compared with 14% of men treated with finasteride. In men treated for up to 2 years, 72% of men in the placebo group demonstrated hair loss, compared with 17% of men treated with finasteride. At 5 years, 100% of men in the placebo group demonstrated hair loss, compared with 35% of men treated with finasteride.

Figure 1:

Patient self-assessment was obtained at each clinic visit from a self-administered questionnaire, which included questions on their perception of hair growth, hair loss, and appearance. This self-assessment demonstrated an increase in amount of hair, a decrease in hair loss, and improvement in appearance in men treated with finasteride. Overall improvement compared with placebo was seen as early as 3 months (p<0.05), with improvement maintained over 5 years.

Investigator assessment was based on a 7-point scale evaluating increases or decreases in scalp hair at each patient visit. This assessment showed significantly greater increases in hair growth in men treated with finasteride compared with placebo as early as 3 months (p<0.001). At 12 months, the investigators rated 65% of men treated with finasteride as having increased hair growth compared with 37% in the placebo group. At 2 years, the investigators rated 80% of men treated with finasteride as having increased hair growth compared with 47% of men treated with placebo. At 5 years, the investigators rated 77% of men treated with finasteride as having increased hair growth, compared with 15% of men treated with placebo.

An independent panel rated standardized photographs of the head in a blinded fashion based on increases or decreases in scalp hair using the same 7-point scale as the investigator assessment. At 12 months, 48% of men treated with finasteride had an increase as compared with 7% of men treated with placebo. At 2 years, an increase in hair growth was demonstrated in 66% of men treated with finasteride, compared with 7% of men treated with placebo. At 5 years, 48% of men treated with finasteride demonstrated an increase in hair growth, 42% were rated as having no change (no further visible progression of hair loss from baseline) and 10% were rated as having lost hair when compared to baseline. In comparison, 6% of men treated with placebo demonstrated an increase in hair growth, 19% were rated as having no change and 75% were rated as having lost hair when compared to baseline.

A 48-week, placebo-controlled study designed to assess by phototrichogram the effect of finasteride on total and actively growing (anagen) scalp hairs in vertex baldness enrolled 212 men with androgenetic alopecia. At baseline and 48 weeks, total and anagen hair counts were obtained in a 1-cm 2 target area of the scalp. Men treated with finasteride showed increases from baseline in total and anagen hair counts of 7 hairs and 18 hairs, respectively, whereas men treated with placebo had decreases of 10 hairs and 9 hairs, respectively. These changes in hair counts resulted in a between-group difference of 17 hairs in total hair count (p<0.001) and 27 hairs in anagen hair count (p<0.001), and an improvement in the proportion of anagen hairs from 62% at baseline to 68% for men treated with finasteride.

Other Results in Vertex Baldness Studies

A sexual function questionnaire was self-administered by patients participating in the two vertex baldness trials to detect more subtle changes in sexual function. At Month 12, statistically significant differences in favor of placebo were found in 3 of 4 domains (sexual interest, erections, and perception of sexual problems). However, no significant difference was seen in the question on overall satisfaction with sex life.

In one of the two vertex baldness studies, patients were questioned on non-scalp body hair growth. Finasteride did not appear to affect non-scalp body hair.

Study in Men with Hair Loss in the Anterior Mid-Scalp Area

A study of 12-month duration, designed to assess the efficacy of finasteride in men with hair loss in the anterior mid-scalp area, also demonstrated significant increases in hair count compared with placebo. Increases in hair count were accompanied by improvements in patient self-assessment, investigator assessment, and ratings based on standardized photographs. Hair counts were obtained in the anterior mid-scalp area, and did not include the area of bitemporal recession or the anterior hairline.

Summary of Clinical Studies in Men

Clinical studies were conducted in men aged 18 to 41 with mild to moderate degrees of androgenetic alopecia. All men treated with finasteride or placebo received a tar-based shampoo (Neutrogena T/Gel® Shampoo) during the first 2 years of the studies. Clinical improvement was seen as early as 3 months in the patients treated with finasteride and led to a net increase in scalp hair count and hair regrowth. In clinical studies for up to 5 years, treatment with finasteride slowed the further progression of hair loss observed in the placebo group. In general, the difference between treatment groups continued to increase throughout the 5 years of the studies.

Ethnic Analysis of Clinical Data from Men

In a combined analysis of the two studies on vertex baldness, mean hair count changes from baseline were 91 vs -19 hairs (finasteride vs placebo) among Caucasians (n=1185), 49 vs -27 hairs among Blacks (n=84), 53 vs -38 hairs among Asians (n=17), 67 vs 5 hairs among Hispanics (n=45) and 67 vs -15 hairs among other ethnic groups (n=20). Patient self-assessment showed improvement across racial groups with finasteride treatment, except for satisfaction of the frontal hairline and vertex in Black men, who were satisfied overall.

14.2 Study in Women

In a study involving 137 postmenopausal women with androgenetic alopecia who were treated with finasteride (n=67) or placebo (n=70) for 12 months, effectiveness could not be demonstrated. There was no improvement in hair counts, patient self-assessment, investigator assessment, or ratings of standardized photographs in the women treated with finasteride when compared with the placebo group [see INDICATIONS AND USAGE (1)].

"See FDA-APPROVED PATIENT LABELING (PATIENT INFORMATION)"